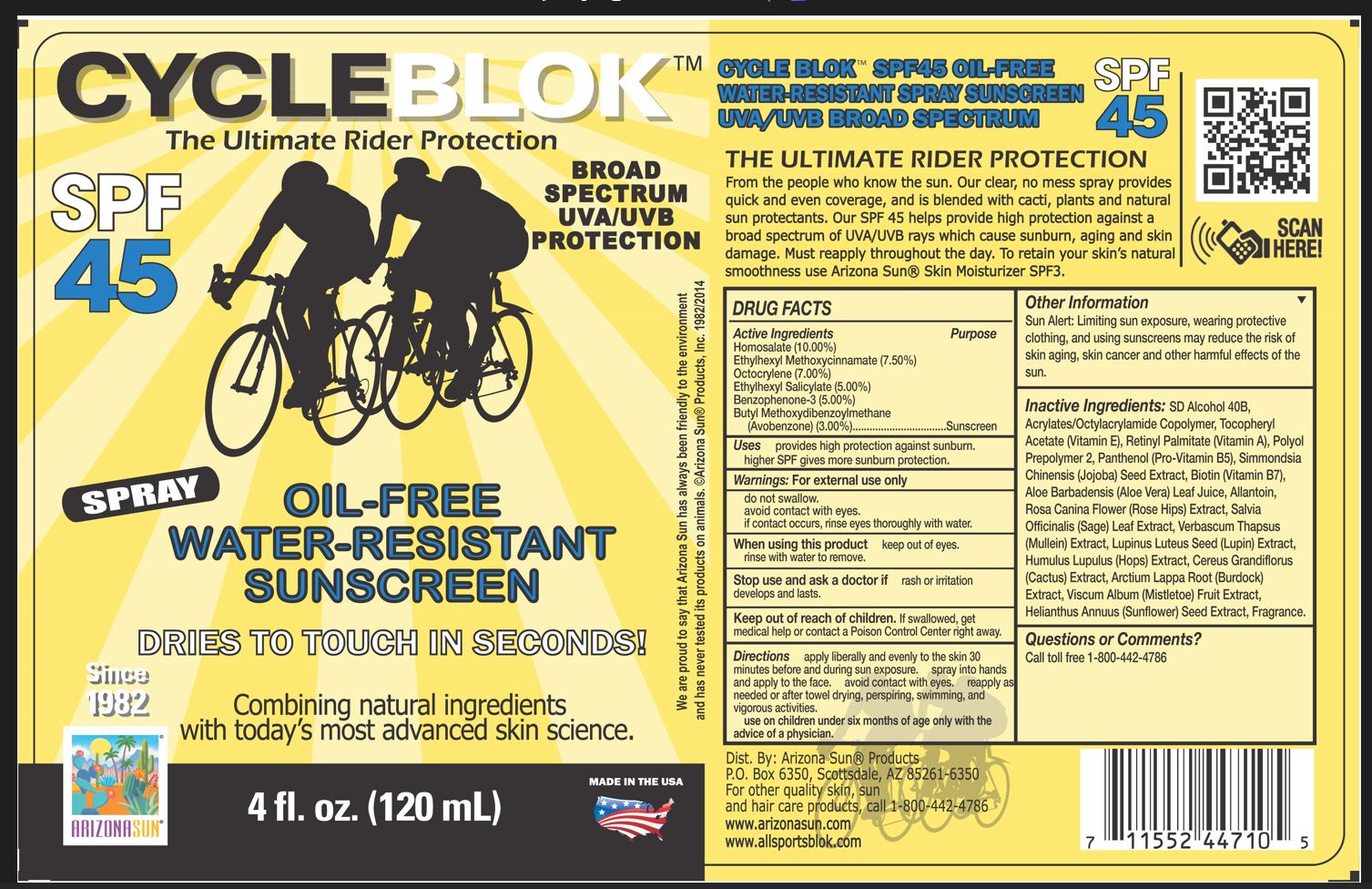 DRUG LABEL: Arizona Sun SPF 45 Cycleblok Sunscreen
NDC: 61973-110 | Form: SPRAY
Manufacturer: Arizona Sun Products
Category: otc | Type: HUMAN OTC DRUG LABEL
Date: 20240221

ACTIVE INGREDIENTS: HOMOSALATE 100 mg/1 g; OXYBENZONE 50 mg/1 g; OCTISALATE 50 mg/1 g; OCTOCRYLENE 70 mg/1 g; OCTINOXATE 75 mg/1 g; AVOBENZONE 30 mg/1 g
INACTIVE INGREDIENTS: SIMMONDSIA CHINENSIS SEED; LUPINUS LUTEUS SEED; HOPS; MULLEIN LEAF; BIOTIN; ROSA CANINA FLOWER; SUNFLOWER SEED; ALCOHOL; VITAMIN A PALMITATE; ALOE VERA LEAF; ALLANTOIN; SELENICEREUS GRANDIFLORUS FLOWER; ACRYLATE/ISOBUTYL METHACRYLATE/N-TERT-OCTYLACRYLAMIDE COPOLYMER (40000 MW); ARCTIUM LAPPA ROOT; SAGE; PANTHENOL; VISCUM ALBUM FRUIT; .ALPHA.-TOCOPHEROL ACETATE; PPG-12/SMDI COPOLYMER

Arizona Sun SPF 45 Cycleblok Sunscreen

Active Ingredients

Homosalate (10.00%), Ethylhexyl Methoxycinnamate (7.50%), Octocrylene (7.00%), Ethylhexyl Salicylate (5.00%), Benzophenone-3 (5.00%), Butyl Methoxydibenzoylmethane (Avobenzone) (3.00%)

Purpose

Sunscreen

Uses

Provides high sunburn protection. Higher SPF gives more sunburn protection

Warnings

For external use only. Do not swallow. Avoid contact with eyes. If contact occurs, rinse eyes thouroughly with water.

When using this product

keep out of eyes. Rinse with water to remove.

Stop use and ask a doctor

if rash or irritation develops and lasts.

Keep out of the reach of children.

If swallowed get medical help or contact a poison control center right away.

Directions

Apply liberally and evenly to the skin 30 minutes before and during sun exposure. Spray into hands and apply to the face. Avoid contact with eyes. Reapply as needed or after towel drying, perspiring, swimming, and vigorous activities. Use on children under six months of age only wih the advise of a physician.

Other Information

Sun Alert: Limiting sun exposure, wearing protective clothing, and using suscreen may reduce the risk of skin aging, skin cancer and other harmful effects of the sun.

Inactive Ingredients

SD Alcohol 40B, Acrylates/ Octylacrylamide Copolymer, Tocopheryl Acetate (Vitamin E), Retinyl Palmitate, Polyol Prepolymer 2, Panthenol, Simmondsia Chinensis (Jojoba) Seed Extract, Biotin, Aloe Barbadensis (Aloe Vera) Leaf Juice, Allantoin, Rosa Canina Flower (Rose Hips) Extract, Salvia Officinalis (Sage) Leaf Extract, Verbascum Thapsus (Mullein) Extract, Lupinus Luteus Seed (Lupin) Extract, Humulus Lupulus (Hops) Extract, Cereus Grandiflorus (Cactus) Extract, Arctium Lappa Root (Burdock) Extract, Viscum Album (Mistletoe) Fruit Extract, Helianthus Annuus (Sunflower) Seed Extract, Fragrance

Questions or Comments?

Call toll free 1-800-442-4786